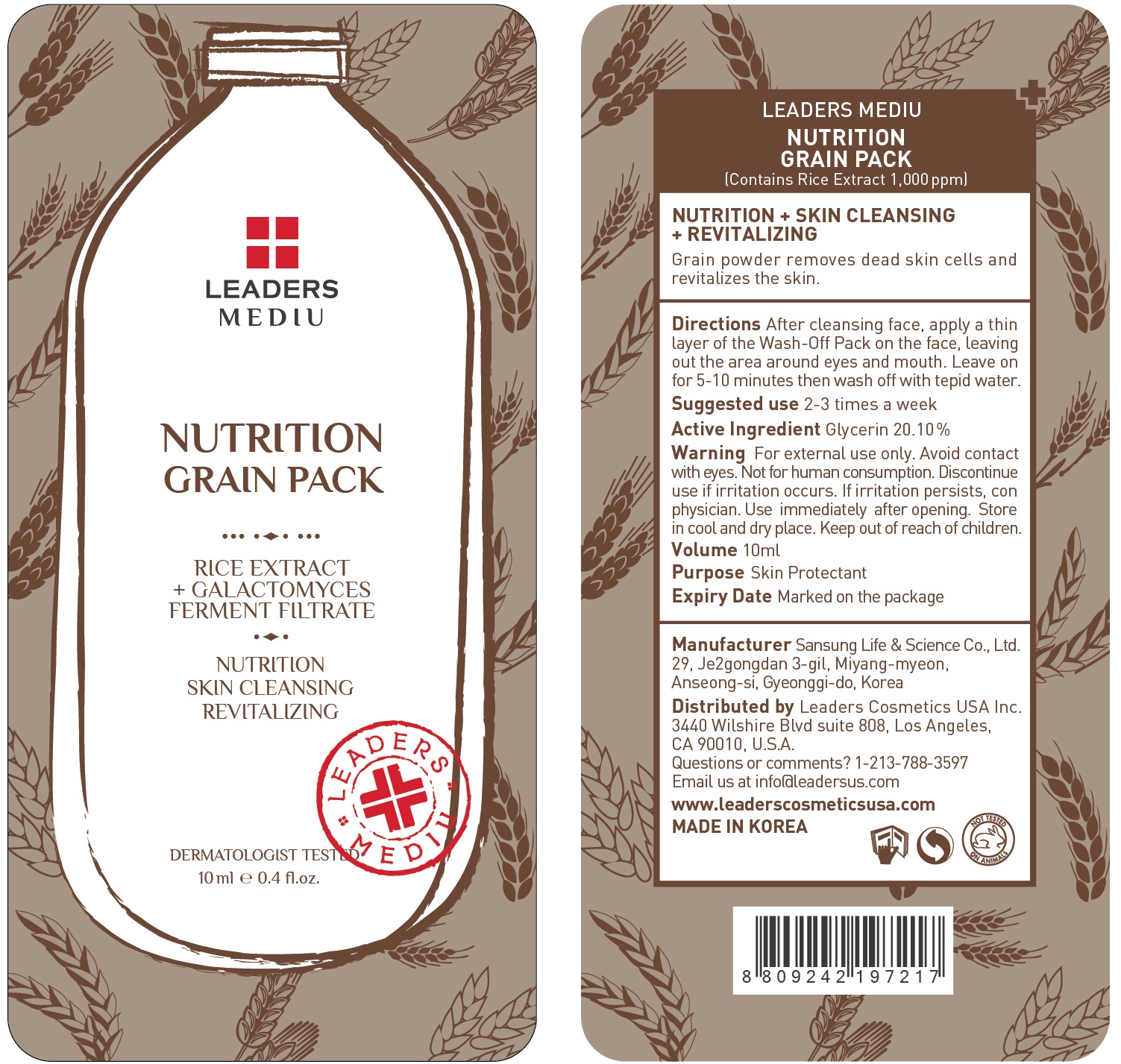 DRUG LABEL: Leaders Mediu Nutrition Grain Pack
NDC: 69424-520 | Form: GEL
Manufacturer: SANSUNG LIFE & SCIENCE CO., LTD.
Category: otc | Type: HUMAN OTC DRUG LABEL
Date: 20160201

ACTIVE INGREDIENTS: Glycerin 2.01 g/10 mL
INACTIVE INGREDIENTS: Water; Butylene Glycol

ACTIVE INGREDIENT

Active Ingredient: Glycerin 20.10%

INACTIVE INGREDIENT

Inactive Ingredients: Water, Butylene Glycol, Cellulose, Alcohol, 1,2-Hexanediol, Arginine, Carbomer, PEG-60 Hydrogenated Castor Oil, Allantoin, Caramel, Fragrance, Oryza sativa (Rice) Extract, Trideceth-10, Prunus armeniaca (Apricot) Seed Powder, Angelica gigas Root Extract, Cornus officinalis Fruit Extract, Panax ginseng Root Extract, Disodium EDTA, Morus alba Bark Extract, Inula Helenium Extract, Galactomyces Ferment Filtrate, CI 15985, CI 17200, CI 42090

PURPOSE

Purpose: Skin Protectant

WARNINGS

Warnings: For external use only. Avoid contact with eyes. Not for human consumption. Discontinue use if irritation occurs. If irritation persists, consult a physician.

Use immediately after opening. Store in cool and dry place. Keep out of reach of children.

KEEP OUT OF REACH OF CHILDREN

Directions

Directions: After cleansing face, apply a thin layer of the Wash-Off Pack on the face, leaving out the area around eyes and mouth. Leave on for 5-10 minutes then wash off with tepid water. *Suggested use is 2-3 times a week

Directions

Directions: After cleansing face, apply a thin layer of the Wash-Off Pack on the face, leaving out the area around eyes and mouth. Leave on for 5-10 minutes then wash off with tepid water. *Suggested use is 2-3 times a week